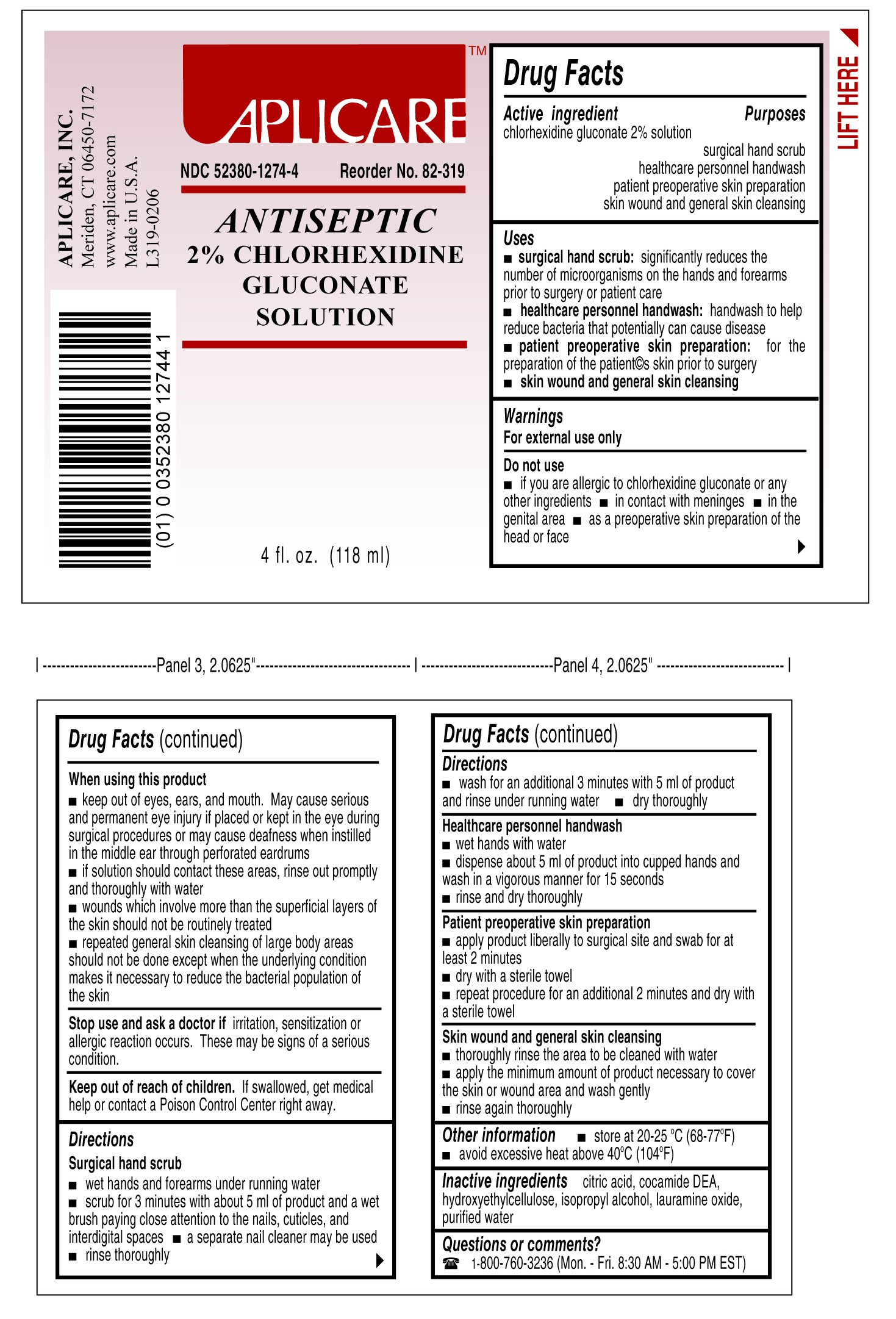 DRUG LABEL: Aplicare Antiseptic Chlorhexidine Gluconate
NDC: 52380-1274 | Form: SOLUTION
Manufacturer: Aplicare, Inc.
Category: otc | Type: HUMAN OTC DRUG LABEL
Date: 20100609

ACTIVE INGREDIENTS: Chlorhexidine Gluconate 2 g/100 g
INACTIVE INGREDIENTS: Anhydrous Citric Acid; Cocamide Diethanolamine; Hydroxyethyl Cellulose (140 CPS AT 5%); Isopropyl Alcohol; Lauramine Oxide; Water

Drug Facts

Active ingredient

Chlorhexidine Gluconate 2% solution

Purpose

Surgical hand scrub

Healthcare personnel handwash

Patient preoperative skin preparation

Skin wound and general skin cleansing

Warning
For external use only

Do not use

- if you are allergic to chlorhexidine gluconate or any other ingredients
- in contact with meninges
- in the genital area
- as a preoperative skin prep of the head or face

When using this product

- keep out of eyes, ears and mouth. May cause serious and permanent eye injury if placed or kept in the eye during surgical procedures or may cause deafness when installed in the middle ear through perforated ear drums.
- if solution should contact these areas, rinse out promptly and thoroughly with water
- wounds which involve more than the superficial layers of the skin should not be routinely treated
- repeated general skin cleansing of large body areas should not be done except when the underlying condition makes it necessary to reduce the bacterial population of the skin

Stop use and ask a doctor if irritation, sensitization or allergic reaction occurs. This may be signs of a serious condition.

Keep out of reach of children. If swallowed, get medical help or contact a Poison Control Center right away.

Directions

Surgical hand scrub

- wet hands and forearms under running water
- scrub for 3 minutes with about 5 ml of product and a wet brush paying close attention to the nails, cuticles and interdigital spaces
- a separate nail cleaner may be used
- rinse thoroughly
- wash for an additional 3 minutes with 5 ml of product and rinse under running water
- dry thoroughly

Healthcare personnel handwash

- wet hands with water
- dispense about 5 ml of product into cupped hands and wash in a vigorous manner for 15 seconds
- rinse and dry thoroughly

Patient preoperative skin preparation

- apply product liberally to surgical site and swab for at least 2 minutes
- dry with a sterile towel
- repeat procedure for an additional 2 minutes and dry with a sterile towel

Skin wound and general skin cleansing

- thoroughly rinse the area to be cleaned with water
- apply the minimum amount of product necessary to cover the skin or wound area and wash gently
- rinse again thoroughly

Questions or comments?

1-800-760-3236 (Mon.-Fri. 8:30AM - 5:00 PM EST)

PACKAGE LABEL

2% Chlorhexidine Gluconate, 4 oz.